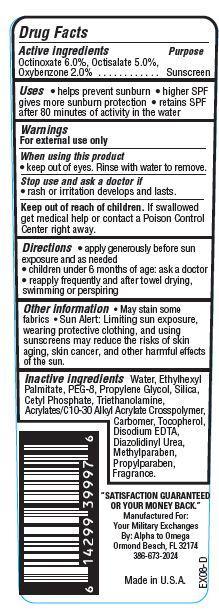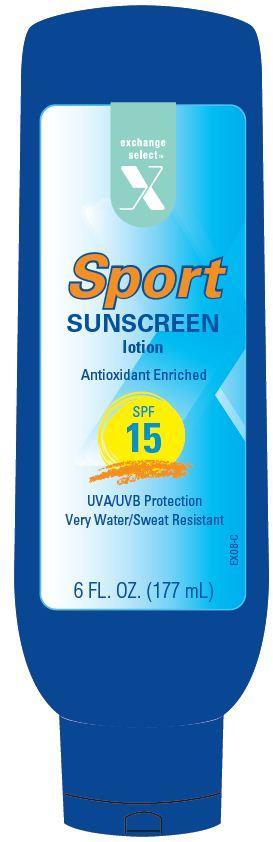 DRUG LABEL: Exchange Select Sport Sunscreen
NDC: 55301-002 | Form: LOTION
Manufacturer: ARMY AND AIR FORCE EXCHANGE SERVICE
Category: otc | Type: HUMAN OTC DRUG LABEL
Date: 20121115

ACTIVE INGREDIENTS: OCTINOXATE 6 g/100 g; OCTISALATE 5 g/100 g; OXYBENZONE 2 g/100 g
INACTIVE INGREDIENTS: WATER; ETHYLHEXYL PALMITATE; POLYETHYLENE GLYCOL 400; PROPYLENE GLYCOL; SILICON DIOXIDE; CETYL PHOSPHATE; TOCOPHEROL; TROLAMINE; DIAZOLIDINYL UREA; TOCOPHEROL; EDETATE DISODIUM

Drug Facts

Active Ingredients

Octinoxate 6.0%
Octisalate 5.0%
Oxybenzone 2.0%

Purpose

Sunscreen

Uses

- helps prevent sunburn
- higher SPF gives more sunburn protection
- retains SPF after 80 minutes of activity in the water

Warnings

For external use only

When using this product

- keep out of eyes. Rinse with water to remove

Stop use and ask a doctor if

- rash or irritation develops and lasts.

Keep Out of the reach of children.

If swallowed get medical help or contact a Poison Control Center right away.

Directions

- apply generously before sun exposure and as needed
- children under 6 months of age:ask a doctor
- reapply frequently and after towel drying, swimming or perspiring.

Other Information

- May stain some fabrics
- Sun Alert: Limiting sun exposure, wearing protective clothing, and using sunscreens may reduce the risks of skin aging, skin cance, and other harmful effects of the sun.

Inactive Ingredients

Water, Ethylhexyl Palmitate, PEG-8, Propylene Glycol, Silica, Cetyl Phosphate, Triethanolamine, Acrylates/C10-30 Alkyl Acrylate Crosspolymer, Carbomer, Tocopherol, Disodium EDTA, Diazolidinyl Urea, Methylparaben, Propylparaben, Fragrance.

Principal Display Panel

exchange
select
X

Sport

SUNSCREEN
lotion

Antioxidant Enriched

SPF
45
UVA/UVB Protection
Very Water Resistant
6 FL. OZ. (177 mL)